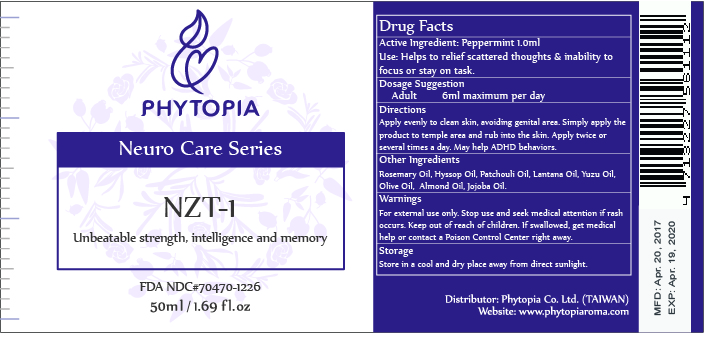 DRUG LABEL: NZT-1
NDC: 70470-1226 | Form: OIL
Manufacturer: Phytopia Co., Ltd.
Category: otc | Type: HUMAN OTC DRUG LABEL
Date: 20170105

ACTIVE INGREDIENTS: MENTHOL 100 mg/50 mL
INACTIVE INGREDIENTS: ALMOND OIL; CITRUS MAXIMA FRUIT RIND OIL; JOJOBA OIL; OLIVE OIL; LANTANA CAMARA LEAF VOLATILE OIL; HYSSOP OIL; ROSEMARY OIL; PATCHOULI OIL

Drug Facts

Active Ingredient: Peppermint 1000mg

Use

Helps to relief scattered thoughts & inability to focus or stay on task.

Dosage Suggestion

Adult 6ml maximum per day

Directions

Apply evenly to clean skin, avoiding genital area. Simply apply the product to temple area and rub into the skin. Apply twice or several times a day. May help ADHD behaviors.

Warnings

For external use only. Stop use and ask doctor if rash occurs. Keep out reach of children.

Other Information

Protect this product from excessive heat

and direct sun.

Warnings

For external use only. Stop use and ask doctor if rash occurs. Keep out reach of children.

INACTIVE INGREDIENT

Other Ingredients:

Rosemary Oil, Hyssop Oil. Patchouli Oil. Latana Oil, Yuzu Oil, Olive Oil, Almond Oil, Jojoba Oil